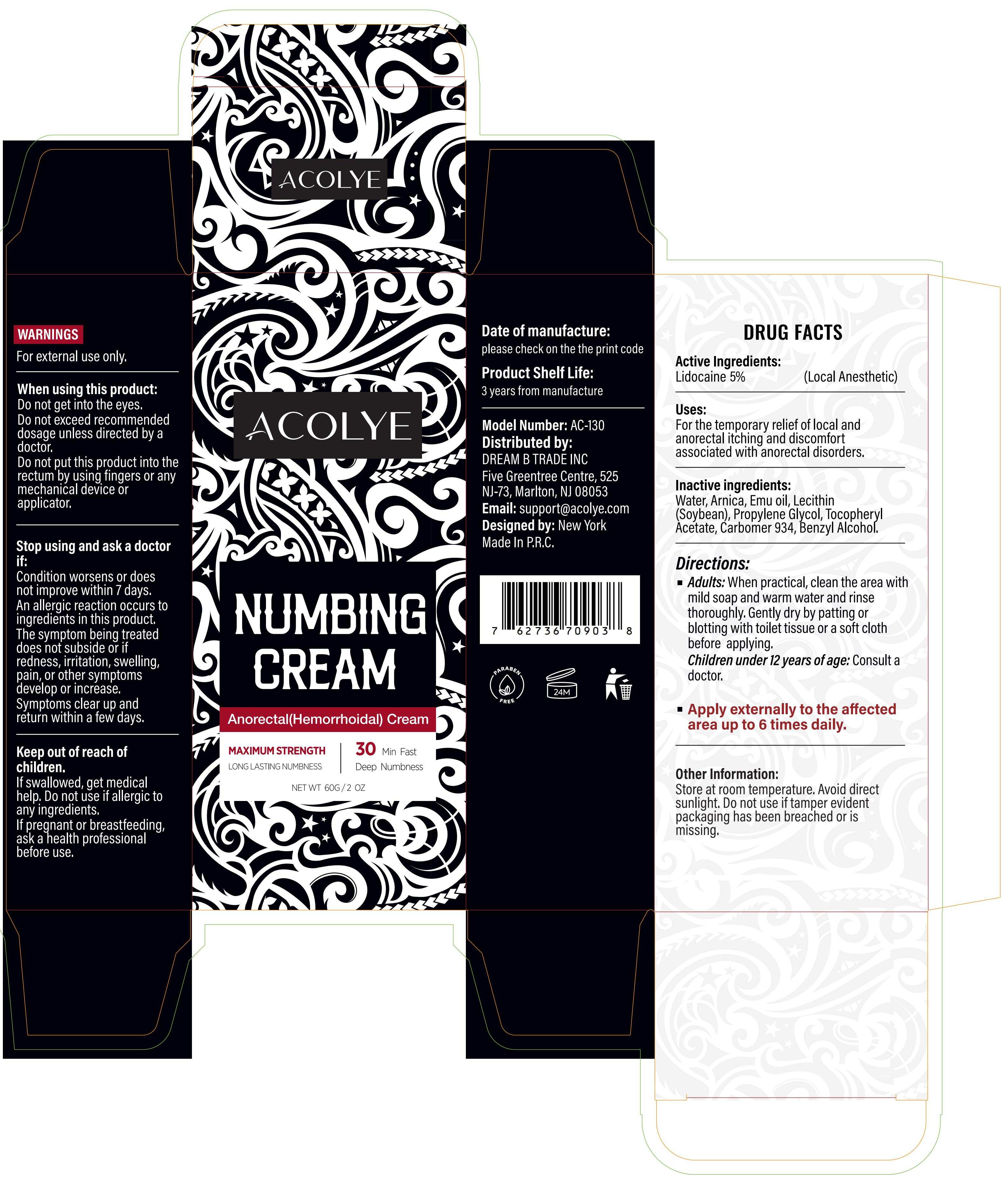 DRUG LABEL: Acolye Numbing Cream  Anorectal(Hemorrhoidal) Cream
NDC: 60771-0029 | Form: CREAM
Manufacturer: Guangzhou Haishi Biological Technology Co., Ltd.
Category: otc | Type: HUMAN OTC DRUG LABEL
Date: 20251009

ACTIVE INGREDIENTS: LIDOCAINE 5 g/100 g
INACTIVE INGREDIENTS: WATER; ARNICA MONTANA FLOWER; BENZYL ALCOHOL; PROPYLENE GLYCOL; EMU OIL; LECITHIN, SOYBEAN; CARBOMER 934; .ALPHA.-TOCOPHEROL ACETATE

Active Ingredients

LIDOCAINE 5%

Purpose

For the temporary relief of local and anorectal itching and discomfort associated with anorectal disorders

Uses

Directions
Adults: When practical, clean the area with mild soap and warm water and rinse thoroughly. Gently dry by patting or blotting with toilet tissue or a soft cloth before applying.Children under 12 years of age: Consult a doctor.
Apply externally to the affected area up to 6 times daily.

Warnings

For external use only

Stop Use

Stop using and ask a doctor if:
Condition worsens or does not improve within 7 days.
An allergic reaction occurs to ingredients in this product.
The symptom being treated does not subside or if redness, irritation, swelling, pain, or other symptoms develop or increase.
Symptoms clear up and return within a few days.
Keep out of reach of children.
If swallowed, get medical help.
If pregnant or breastfeeding, ask a health professional before use.

Do Not Use

on damaged or broken skin.

When Using

When using this product:
Do not get into the eyes.
Do not exceed recommended dosage unless directed by a doctor.
Do not put this product into the rectum by using fingers or any mechanical device or applicator.

Keep Out Of Reach Of Children

If swallowed, get medical help or contact a Poison Control Center immediately.

Inactive ingredients

Water: 82%
Arnica: 2%
Emu oil: 2%
Lecithin (Soybean): 2%
Propylene Glycol: 2%
Tocopheryl Acetate: 2%
Carbomer 934: 2%
Benzyl Alcohol: 1%

Dosage & administration

Adults and children 12 years and older: Apply externally to the affected area. APPLY UP TO 6 TIMES DAILY.
Children under 12 years of age: Consult a doctor.